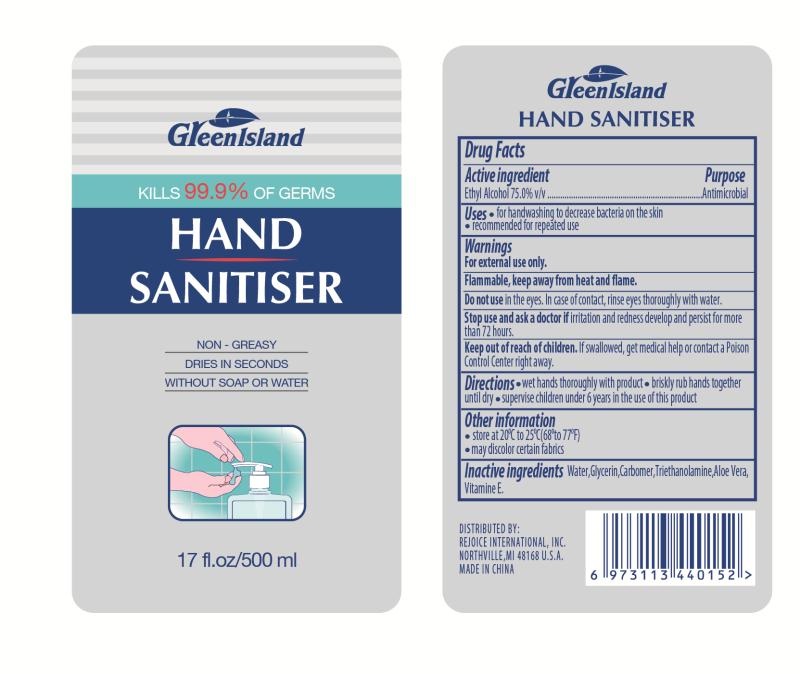 DRUG LABEL: Hand Sanitiser
NDC: 75742-001 | Form: GEL
Manufacturer: Zhejiang Guoyao Jingyue Aerosol Co., Ltd.
Category: otc | Type: HUMAN OTC DRUG LABEL
Date: 20260105

ACTIVE INGREDIENTS: ALCOHOL 75 mL/100 mL
INACTIVE INGREDIENTS: ALOE VERA LEAF; .ALPHA.-TOCOPHEROL; WATER; TROLAMINE; GLYCERIN; CARBOMER 940

Hand Sanitizer

Active Ingredient

Ethyl Alcohol 75.0% v/v

Purpose

Antimicrobial

Uses

- for handwashing to reduce bacteria on the skin
- recommended for repeated use

Warnings

For external use only.

Flammable, keep away from heat and flame.

Do not use in the eyes. In case of contact, rinse eyes thoroughly with water.

Stop use and ask a doctor if irritation and redness develop and persist for more than 72 hours.

Keep out of reach of children. If swallowed, get medical help or contact a Poison Control Center right away.

Directions

• wet hands thoroughly with product • briskly rub hands together until dry • supervise children under 6 years in the use of this product

Other information

- store at 20ºC to 25ºC (68º to 77ºF)
- may discolor certain fabrics

Inactive Ingredients

Water, glycerin, carbomer, triethanolamine, aloe vera, vitamine E